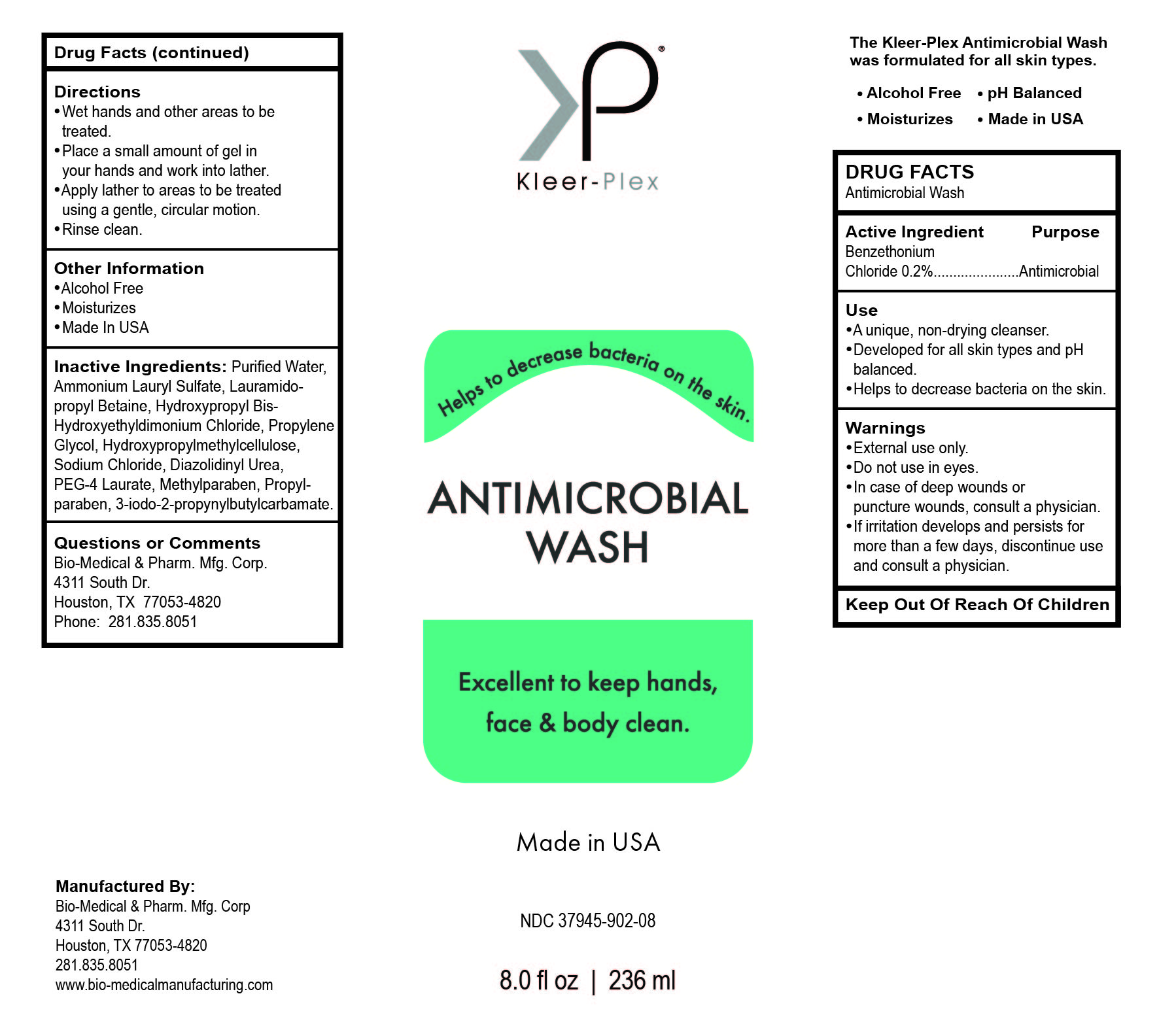 DRUG LABEL: ANTIMICROBIAL FACE BODY WASH
NDC: 37945-902 | Form: LIQUID
Manufacturer: Bio-Medical & Pharmaceutical Manufacturing Corporation
Category: otc | Type: HUMAN OTC DRUG LABEL
Date: 20200415

ACTIVE INGREDIENTS: BENZETHONIUM CHLORIDE 0.2 g/100 g
INACTIVE INGREDIENTS: PROPYLENE GLYCOL; LAURAMIDOPROPYL BETAINE; PEG-4 LAURATE; AMMONIUM LAURYL SULFATE; PROPYLPARABEN; IODOPROPYNYL BUTYLCARBAMATE; HYPROMELLOSES; SODIUM CHLORIDE; WATER; HYDROXYPROPYL BIS-HYDROXYETHYLDIMONIUM CHLORIDE; METHYLPARABEN; DIAZOLIDINYL UREA

Drug Facts

Antimicrobial Wash

Active Ingredients

Benzethonium Chloride 0.2%

Purpose

Antimicrobial

Use

A unique, non-drying cleanser.
Developed for all skin types and pH balanced.
Helps to decrease bacteria on the skin.

Warnings

External use only.
Do not use in eyes.
In case of deep wounds or puncture wounds, consult a physician.
If irritation develops and persists for more than a few days, discontinue use and consult a physician.

Keep out of reach of children

If swallowed, get medical help or contact a Poison Control Center immediately. (1-800-222-1222)

Directions

Wet hands and other areas to be treated.
Place a small amount of gel in your hands and work into lather.
Apply lather to areas to be treated using a gentle, circular motion.

Rinse clean.

Other information

Alcohol Free

Moisturizes

Made In USA

Inactive Ingredients

Purified Water, Ammonium Lauryl Sulfate, Lauramidopropyl Betaine, Hydroxypropyl Bis- Hydroxyethyldimonium Chloride, Propylene Glycol, Hydroxypropylmethylcellulose, Sodium Chloride, Diazolidinyl Urea, PEG-4 Laurate, Methylparaben, Propylparaben, 3-iodo-2-propynylbutylcarbamate.

Questions or Comments

Bio-Medical & Pharm. Mfg. Corp.

4311 South Dr.,

Houston, TX 77053-4820

Phone: 281.835.8051